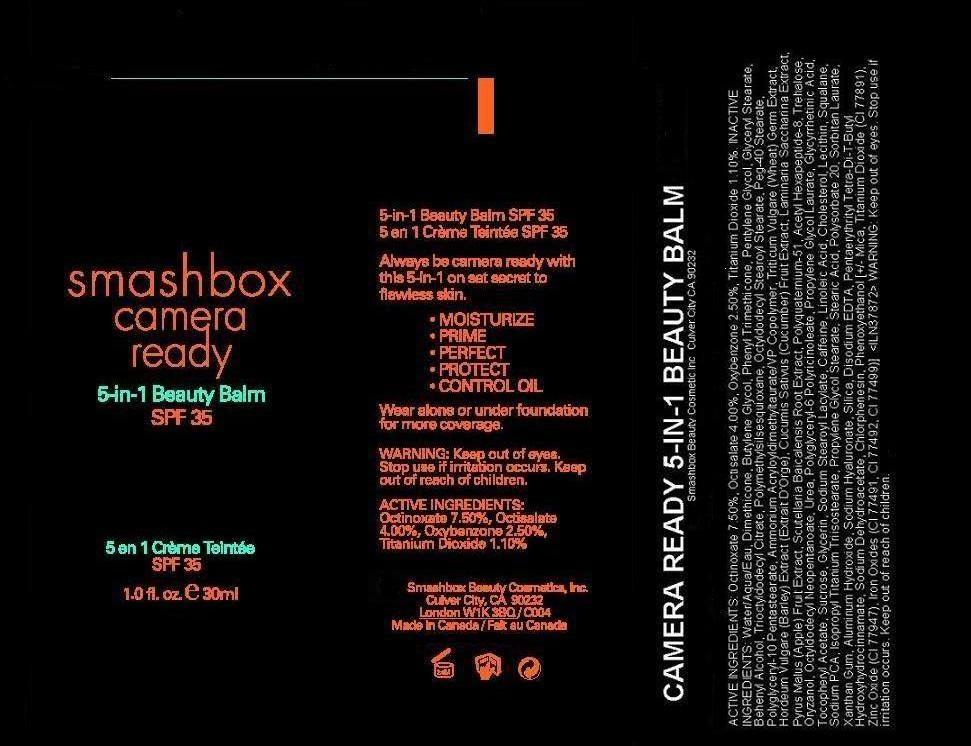 DRUG LABEL: CAMERA READY
NDC: 10348-002 | Form: LIQUID
Manufacturer: SMASHBOX  BEAUTY COSMETICS, INC
Category: otc | Type: HUMAN OTC DRUG LABEL
Date: 20110701

ACTIVE INGREDIENTS: OCTINOXATE 7.5 mL/100 mL; OCTISALATE 4.0 mL/100 mL; OXYBENZONE 2.5 mL/100 mL; TITANIUM DIOXIDE 1.1 mL/100 mL
INACTIVE INGREDIENTS: WATER; DIMETHICONE; BUTYLENE GLYCOL; PHENYL TRIMETHICONE; PENTYLENE GLYCOL; GLYCERYL MONOSTEARATE; DOCOSANOL; POLYMETHYLSILSESQUIOXANE (11 MICRONS); OCTYLDODECYL STEAROYL STEARATE; PEG-40 STEARATE; WHEAT GERM; CUCUMBER; APPLE; SCUTELLARIA BAICALENSIS ROOT; ACETYL HEXAPEPTIDE-3; TREHALOSE; GAMMA ORYZANOL; OCTYLDODECYL NEOPENTANOATE; UREA; PROPYLENE GLYCOL MONOLAURATE; ALPHA-TOCOPHEROL ACETATE; SUCROSE; GLYCERIN; CAFFEINE; LINOLEIC ACID; CHOLESTEROL; LECITHIN, SOYBEAN; SQUALANE; SODIUM PYRROLIDONE CARBOXYLATE; PROPYLENE GLYCOL MONOSTEARATE; STEARIC ACID; POLYSORBATE 20; SORBITAN MONOLAURATE; XANTHAN GUM; ALUMINUM HYDROXIDE; HYALURONATE SODIUM; SILICON DIOXIDE; SODIUM DEHYDROACETATE; CHLORPHENESIN; PHENOXYETHANOL; MICA; FERRIC OXIDE RED

ACTIVE INGREDIENT

ACTIVE INGREDIENTS: OCTINOXATE 7.50% [] OCTISALATE 4.00% [] OXYBENZONE 2.50% [] TITANIUM DIOXIDE 1.10%

INACTIVE INGREDIENT

INACTIVE INGREDIENTS: WATER [] DIMETHICONE [] BUTYLENE GLYCOL [] PHENYL TRIMETHICONE [] PENTYLENE GLYCOL [] GLYCERYL STEARATE [] BEHENYL ALCOHOL [] TRIOCTYLDODECYL CITRATE [] POLYMETHYLSILSESQUIOXANE [] OCTYLDODECYL STEAROYL STEARATE [] PEG-40 STEARATE [] POLYGLYCERYL-10 PENTASTEARATE [] AMMONIUM ACRYLOYLDIMETHYLTAURATE/VP COPOLYMER [] TRITICUM VULGARE (WHEAT) GERM EXTRACT [] HORDEUM VULGARE (BARLEY) EXTRACT [] CUCUMIS SATIVUS (CUCUMBER) FRUIT EXTRACT [] LAMINARIA SACCHARINA EXTRACT [] PYRUS MALUS (APPLE) FRUIT EXTRACT [] SCUTELLARIA BAICALENSIS ROOT EXTRACT [] POLYQUATERNIUM-51 [] ACETYL HEXAPEPTIDE-8 [] TREHALOSE [] ORYZANOL [] OCTYLDODECYL NEOPENTANOATE [] UREA [] POLYGLYCERYL-6 POLYRICINOLEATE [] PROPYLENE GLYCOL LAURATE [] GLYCYRRHETINIC ACID [] TOCOPHERYL ACETATE [] SUCROSE [] GLYCERIN [] SODIUM STEAROYL LACTYLATE [] CAFFEINE [] LINOLEIC ACID [] CHOLESTEROL [] LECITHIN [] SQUALANE [] SODIUM PCA [] ISOPROPYL TITANIUM TRIISOSTEARATE [] PROPYLENE GLYCOL STEARATE [] STEARIC ACID [] POLYSORBATE 20 [] SORBITAN LAURATE [] XANTHAN GUM [] ALUMINUM HYDROXIDE [] SODIUM HYALURONATE [] SILICA [] DISODIUM EDTA [] PENTAERYTHRITYL TETRA-DI-T-BUTYL HYDROXYHYDROCINNAMATE [] SODIUM DEHYDROACETATE [] CHLORPHENESIN [] PHENOXYETHANOL [] [+/- TITANIUM DIOXIDE (CI 77891) [] ZINC OXIDE (CI 77947) [] IRON OXIDES (CI 77491, CI 77492, CI 77499) [] MICA

WARNINGS

WARNING: KEEP OUT OF EYES. STOP USE IF IRRITATION OCCURS.

KEEP OUT OF REACH OF CHILDREN.

PACKAGE LABEL

PRINCIPAL DISPLAY PANEL:

SMASHBOX CAMERA READY

5 IN 1

BEAUTY BALM

SPF 35

1.0 FL OZ/ 30 ML

Smashbox Beauty Cosmetics Inc.

Culver City, California, 90232

made in canada